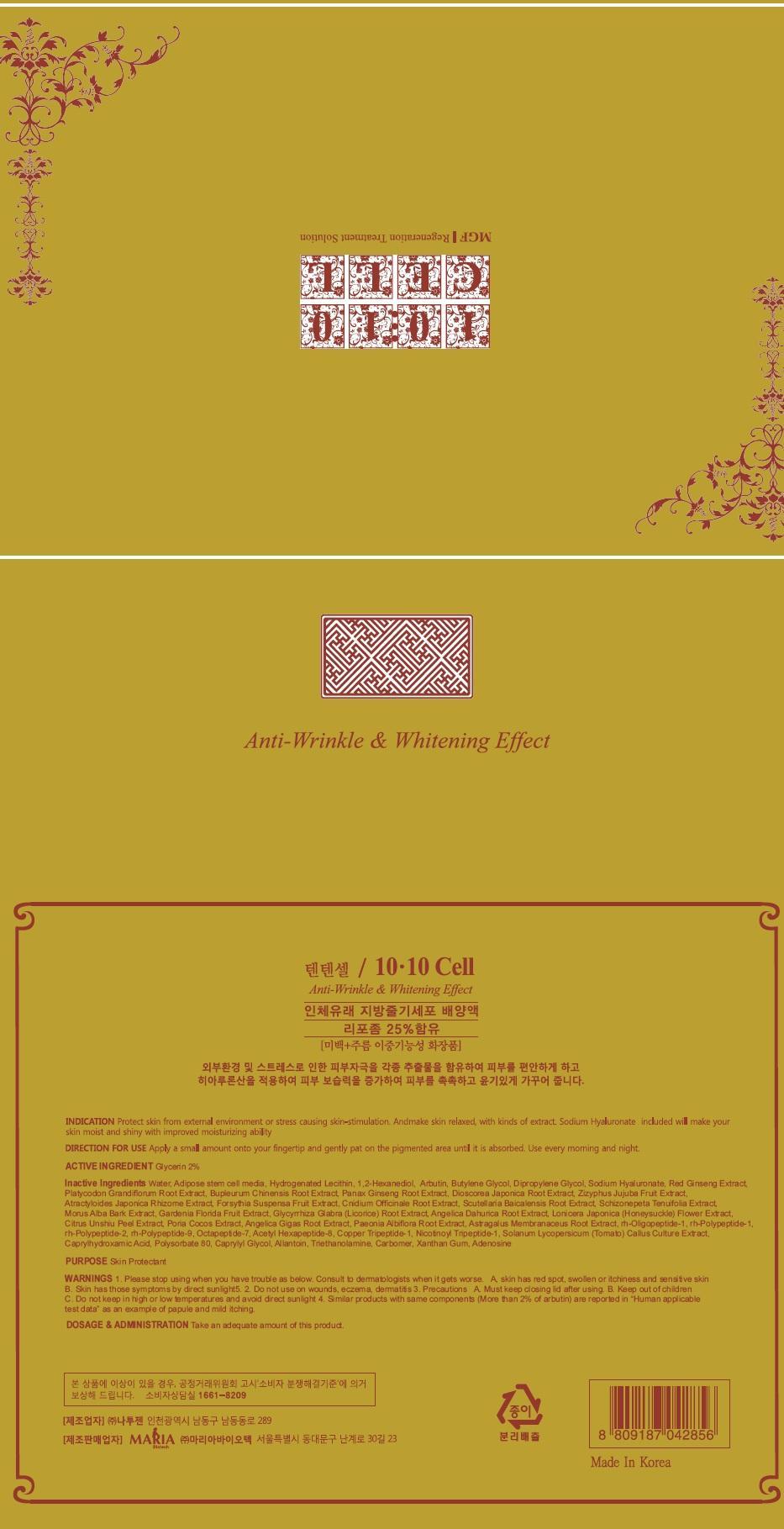 DRUG LABEL: TEN TEN CELL
NDC: 70087-010 | Form: SOLUTION
Manufacturer: MARIA BIOTECH CO., LTD.
Category: otc | Type: HUMAN OTC DRUG LABEL
Date: 20150915

ACTIVE INGREDIENTS: Glycerin 0.12 mg/10 1
INACTIVE INGREDIENTS: Water; Arbutin

ACTIVE INGREDIENT

Active Ingredient: Glycerin 2%

INACTIVE INGREDIENT

Inactive Ingredients: Water, Adipose stem cell media, Hydrogenated Lecithin, 1,2-Hexanediol, Arbutin, Butylene Glycol, Dipropylene Glycol, Sodium Hyaluronate, Red Ginseng Extract, Platycodon Grandiflorum Root Extract, Bupleurum Chinensis Root Extract, Panax Ginseng Root Extract, Dioscorea Japonica Root Extract, Zizyphus Jujuba Fruit Extract, Atractyloides Japonica Rhizome Extract, Forsythia Suspensa Fruit Extract, Cnidium Officinale Root Extract, Scutellaria Baicalensis Root Extract, Schizonepeta Tenuifolia Extract, Morus Alba Bark Extract, Gardenia Florida Fruit Extract, Glycyrrhiza Glabra (Licorice) Root Extract, Angelica Dahurica Root Extract, Lonicera Japonica (Honeysuckle) Flower Extract, Citrus Unshiu Peel Extract, Poria Cocos Extract, Angelica Gigas Root Extract, Paeonia Albiflora Root Extract, Astragalus Membranaceus Root Extract, rh-Oligopeptide-1, rh-Polypeptide-1, rh-Polypeptide-2, rh-Polypeptide-9, Octapeptide-7, Acetyl Hexapeptide-8, Copper Tripeptide-1, Nicotinoyl Tripeptide-1, Solanum Lycopersicum (Tomato) Callus Culture Extract, Caprylhydroxamic Acid, Polysorbate 80, Caprylyl Glycol, Allantoin, Triethanolamine, Carbomer, Xanthan Gum, Adenosine

PURPOSE

Purpose: Skin Protectant

WARNINGS

Warnings: 1. Please stop using when you have trouble as below. Consult to dermatologists when it gets worse. A, skin has red spot, swollen or itchiness and sensational skin B. Skin has those symptoms by direct sunlight.

2. Do not use wounds, eczema, dermatitis

3. Precautions A. Must keep closing lid after using. B. Keep out of children C. Do not keep in high or low temperatures and avoid direct sunlight

4. Similar products with same components (More than 2% of arbutin) are reported in “Human applicable test data” as an example of papule and mild itching.

Keep out of reach of children: Keep out of reach of babies and children.

INDICATIONS & USAGE

Indications & Usage: After washing the face, dispense an appropriate amount into your palm, and evenly apply to the entire face.

DOSAGE & ADMINISTRATION

Dosage & Administration: Take an adequate amount of this product.